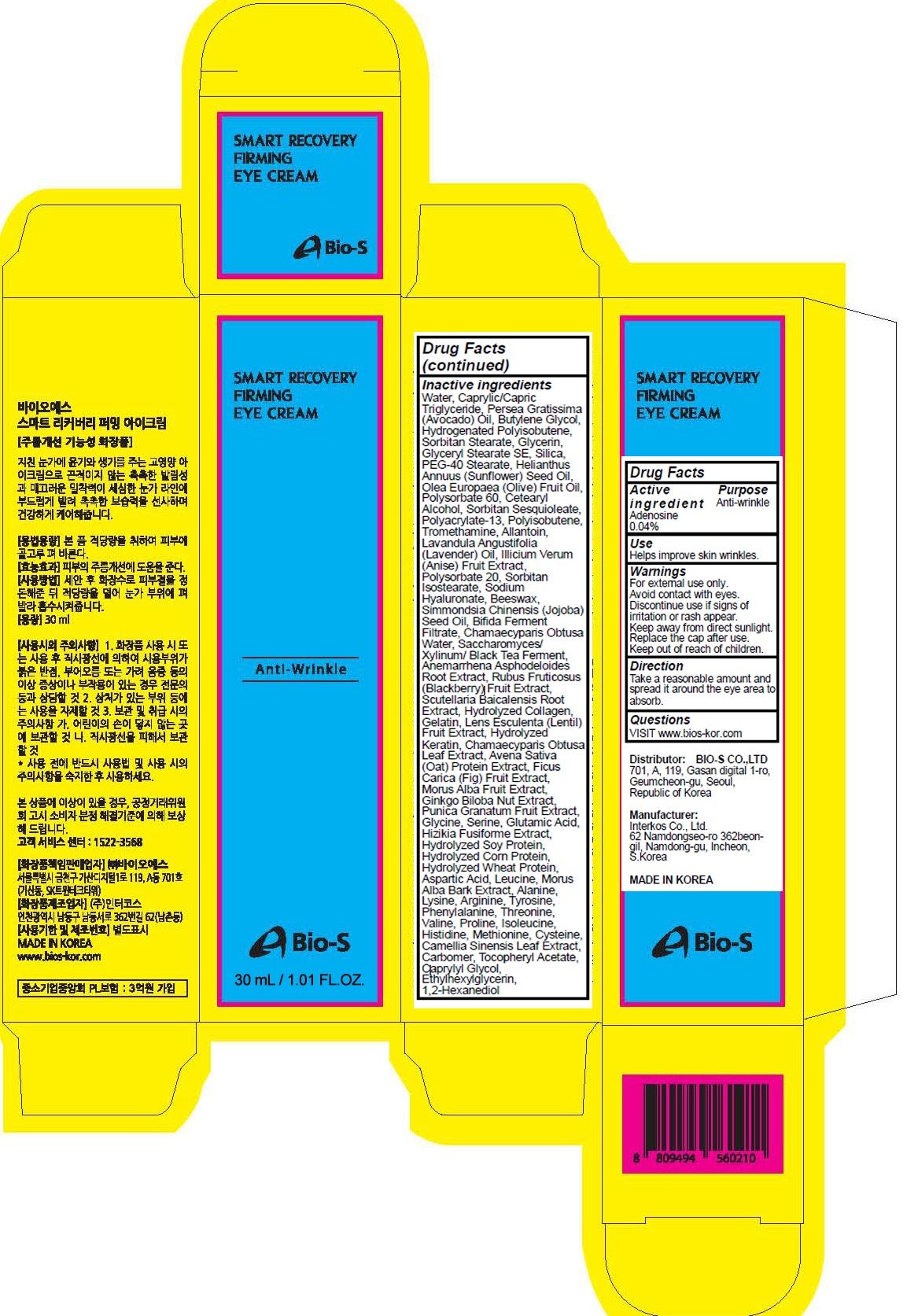 DRUG LABEL: SMART RECOVERY FIRMING EYE
NDC: 81211-030 | Form: CREAM
Manufacturer: BIO-S CO.,LTD
Category: otc | Type: HUMAN OTC DRUG LABEL
Date: 20201210

ACTIVE INGREDIENTS: Adenosine 0.012 g/30 mL
INACTIVE INGREDIENTS: Water; MEDIUM-CHAIN TRIGLYCERIDES; AVOCADO OIL; Butylene Glycol; HYDROGENATED POLYBUTENE (1300 MW)

ACTIVE INGREDIENT

Adenosine 0.04%

PURPOSE

Anti-wrinkle

Use

Helps improve skin wrinkles.

WARNINGS

For external use only.
Avoid contact with eyes.
Discontinue use if signs of irritation or rash appear.
Keep away from direct sunlight.
Replace the cap after use.
Keep out of reach of children.

KEEP OUT OF REACH OF CHILDREN

Direction

Take a reasonable amount and spread it around the eye area to absorb.

QUESTIONS

VISIT www.bios-kor.com

INACTIVE INGREDIENTS

Water, Caprylic/Capric Triglyceride, Persea Gratissima (Avocado) Oil, Butylene Glycol, Hydrogenated Polyisobutene, Sorbitan Stearate, Glycerin, Glyceryl Stearate SE, Silica, PEG-40 Stearate, Helianthus Annuus (Sunflower) Seed Oil, Olea Europaea (Olive) Fruit Oil, Polysorbate 60, Cetearyl Alcohol, Sorbitan Sesquioleate, Polyacrylate-13, Polyisobutene, Tromethamine, Allantoin, Lavandula Angustifolia (Lavender) Oil, Illicium Verum (Anise) Fruit Extract, Polysorbate 20, Sorbitan Isostearate, Sodium Hyaluronate, Beeswax, Simmondsia Chinensis (Jojoba) Seed Oil, Bifida Ferment Filtrate, Chamaecyparis Obtusa Water, Saccharomyces/Xylinum/Black Tea Ferment, Anemarrhena Asphodeloides Root Extract, Rubus Fruticosus (Blackberry) Fruit Extract, Scutellaria Baicalensis Root Extract, Hydrolyzed Collagen, Gelatin, Lens Esculenta (Lentil) Fruit Extract, Hydrolyzed Keratin, Chamaecyparis Obtusa Leaf Extract, Avena Sativa (Oat) Protein Extract, Ficus Carica (Fig) Fruit Extract, Morus Alba Fruit Extract, Ginkgo Biloba Nut Extract, Punica Granatum Fruit Extract, Glycine, Serine, Glutamic Acid, Hizikia Fusiforme Extract, Hydrolyzed Soy Protein, Hydrolyzed Corn Protein, Hydrolyzed Wheat Protein, Aspartic Acid, Leucine, Morus Alba Bark Extract, Alanine, Lysine, Arginine, Tyrosine, Phenylalanine, Threonine, Valine, Proline, Isoleucine, Histidine, Methionine, Cysteine, Camellia Sinensis Leaf Extract, Carbomer, Tocopheryl Acetate, Caprylyl Glycol, Ethylhexylglycerin, 1,2-Hexanediol